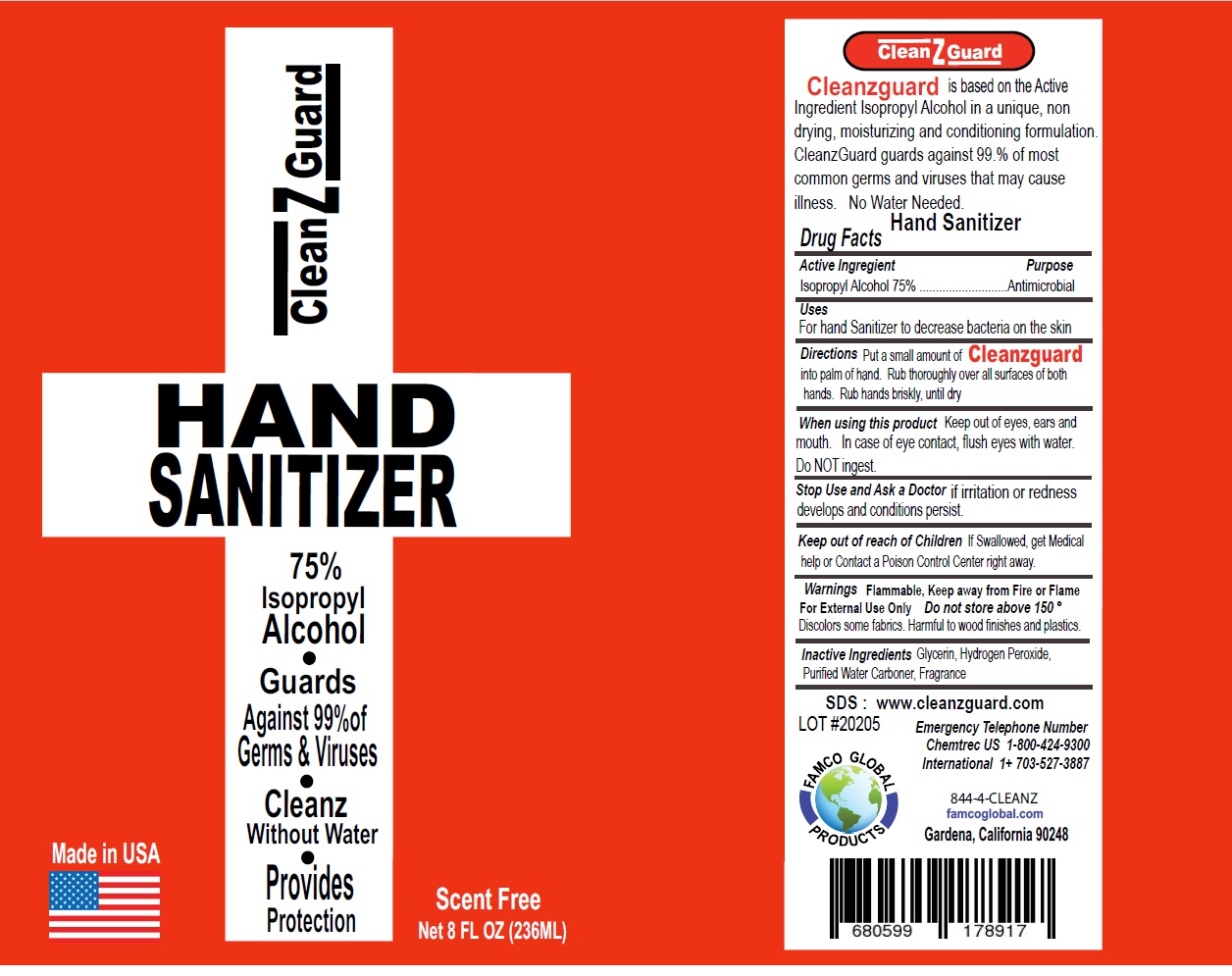 DRUG LABEL: Cleanzguard Hand Sanitizer
NDC: 79743-130 | Form: GEL
Manufacturer: Famco Global Llc
Category: otc | Type: HUMAN OTC DRUG LABEL
Date: 20200724

ACTIVE INGREDIENTS: ISOPROPYL ALCOHOL 75 mL/100 mL
INACTIVE INGREDIENTS: GLYCERIN; HYDROGEN PEROXIDE; WATER; CARBOMER HOMOPOLYMER, UNSPECIFIED TYPE

CleanzGuard HAND SANITIZER

Active Ingredient

Isopropyl Alcohol 75%

Purpose

Antimicrobial

Uses

For hand Sanitizer to decrease bacteria on the skin

DOSAGE AND ADMINISTRATION

Directions Put a small amount of Cleanzguard into palm of hand. Rub thoroughly over all surfaces of both hands. Rub hands briskly, until dry

Warnings Flammable, Keep away from Fire or Flame

For External Use Only

Discolors some fabrics. Harmful to wood finishes and plastics.

When using this product Keep out of eyes, ears and mouth. In case of eye contact, flush eyes with water.

Do NOT ingest.

Stop Use and Ask a Doctor if irritation or redness develops and conditions persist.

Keep out of reach of Children If Swallowed, get Medical help or Contact a Poison Control Center right away.

STORAGE AND HANDLING

Do not store above 150 °

INACTIVE INGREDIENT

Inactive Ingredients Glycerin, Hydrogen Peroxide, Purified Water Carbomer, Fragrance

• Guards Against 99%of Germs & Viruses

• Cleanz Without Water

• Provides Protection

Made in USA

Scent Free

Cleanzguard is based on the Active Ingredient Isopropyl Alcohol in a unique, non drying, moisturizing and conditioning formulation. CleanzGuard guards 99.% of most common germs that may cause illness, in just 15 seconds. No Water Needed.

SDS : www.cleanzguard.com

Emergency Telephone Number

Chemtrec US 1-800-424-9300

International 1+ 703-527-3887

FAMCO GLOBAL PRODUCTS

844-4-CLEANZ

famcoglobal.com

Gardena, California 90248